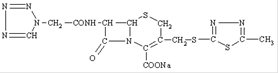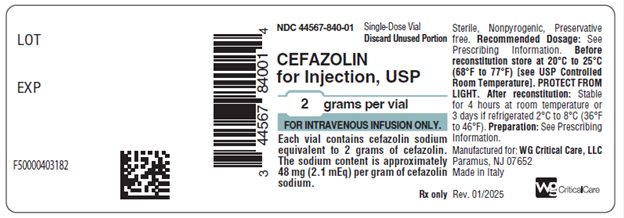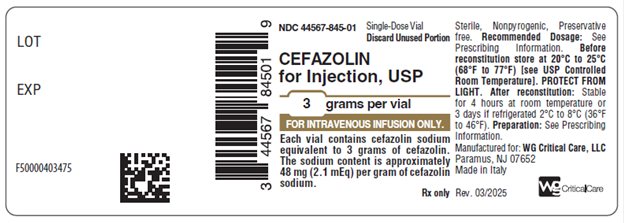 DRUG LABEL: Cefazolin
NDC: 44567-840 | Form: INJECTION, POWDER, FOR SOLUTION
Manufacturer: WG Critical Care, LLC
Category: prescription | Type: HUMAN PRESCRIPTION DRUG LABEL
Date: 20240331

ACTIVE INGREDIENTS: CEFAZOLIN SODIUM 2 g/1 1

HIGHLIGHTS OF PRESCRIBING INFORMATION

These highlights do not include all the information needed to use CEFAZOLIN FOR INJECTION safely and effectively. See full prescribing information for CEFAZOLIN FOR INJECTION. [Pediatric use information is approved for B. Braun Medical’s Cefazolin for Injection and Dextrose for Injection. However, due to B. Braun Medical’s marketing exclusivity rights, this drug product is not labeled with that pediatric information.]
CEFAZOLIN for injection, for intravenous use.
Initial U.S. Approval: 1973

RECENT MAJOR CHANGES

Dosage and Administration (2.1) 3/2024

1 INDICATIONS AND USAGE

Cefazolin for Injection is a cephalosporin antibacterial indicated for perioperative prophylaxis in adult patients (1.1).

To reduce the development of drug-resistant bacteria and maintain the effectiveness of Cefazolin for Injection and other antibacterial drugs, Cefazolin for Injection should be used only to treat or prevent infections that are proven or strongly suspected to be caused by bacteria. (1.2)

2 DOSAGE AND ADMINISTRATION

- For intravenous infusion only administered over approximately 30 minutes. (2.1)
- Not for intravenous bolus administration or intramuscular administration. (2.1)

Table 1: Recommended Dosage for Perioperative Prophylaxis in Adults with CLcr Equal to 55 mL/min or Greater (2.2)
Dose administered; ½ hour to 1 hour prior to the start; of surgery | Additional dose during lengthy operative procedures (e.g., 2 hours or more) | Dose for 24 hours postoperatively
1 gram (g) to 2 g | 500 mg to 1 g | 500 mg to 1 g every 6 hours to 8 hours

- Dosage adjustment is required for adult patients with CLcr that is less than 55 mL/min. (2.3 and 8.6)
- See full prescribing information for preparation and administration instructions. (2.4)

3 DOSAGE FORMS AND STRENGTHS

- For Injection: 2 grams or 3 grams of cefazolin as a powder in a single-dose vial for reconstitution. (3)

4 CONTRAINDICATIONS

- Hypersensitivity to cefazolin or other cephalosporin class antibacterial drugs, penicillins, or other beta-lactams (4.1)

5 WARNINGS AND PRECAUTIONS

- Hypersensitivity Reactions: Cross-hypersensitivity may occur in up to 10% of patients with a history of penicillin allergy. If an allergic reaction occurs, discontinue the drug. (5.1)
- Clostridioides difficile-associated diarrhea (CDAD): May range from mild diarrhea to fatal colitis. Evaluate if diarrhea occurs. (5.3)
- Prothrombin Activity: May be associated with a fall in prothrombin activity. Prothrombin time should be monitored in patients at risk and exogenous vitamin K administered as indicated (5.5)

6 ADVERSE REACTIONS

1. Adult Patients: Most common adverse reactions: gastrointestinal (nausea, vomiting, diarrhea), and allergic reactions (anaphylaxis, urticaria, skin rash). (6)

To report SUSPECTED ADVERSE REACTIONS, contact WG Critical Care, LLC at 1-866-562-4708 or FDA at 1-800-FDA-1088 or www.fda.gov/medwatch.

7 DRUG INTERACTIONS

- Probenecid: The renal excretion of cefazolin is inhibited by probenecid. Co-administration of probenecid with Cefazolin for Injection is not recommended. (7)

FULL PRESCRIBING INFORMATION

1 INDICATIONS AND USAGE

1.1 Perioperative Prophylaxis

Cefazolin for Injection is indicated for perioperative prophylaxis in adult patients [see Dosage and Administration (2.1, 2.2, 2.3, 2.4).

The perioperative use of Cefazolin for Injection is indicated in adult surgical patients in whom infection at the operative site would present a serious risk (e.g., during open-heart surgery and prosthetic arthroplasty).

The prophylactic administration of Cefazolin for Injection preoperatively, intraoperatively and postoperatively may reduce the incidence of certain postoperative infections in patients undergoing surgical procedures which are classified as contaminated or potentially contaminated (e.g., vaginal hysterectomy, and cholecystectomy in high-risk patients such as those older than 70 years, with acute cholecystitis, obstructive jaundice or common duct bile stones).

Pediatric use information is approved for B. Braun Medical’s Cefazolin for Injection and Dextrose for Injection. However, due to B. Braun Medical’s marketing exclusivity rights, this drug product is not labeled with that pediatric information.

1.2 Usage

To reduce the development of drug-resistant bacteria and maintain the effectiveness of Cefazolin for Injection USP and other antibacterial drugs, Cefazolin for Injection USP should be used only to treat or prevent infections that are proven or strongly suspected to be caused by susceptible bacteria. When culture and susceptibility information are available, they should be considered in selecting or modifying antibacterial therapy. In the absence of such data, local epidemiology and susceptibility patterns may contribute to the empiric selection of therapy.

2 DOSAGE AND ADMINISTRATION

2.1 Important Administration Instructions

Administer Cefazolin for Injection via intravenous infusion only over approximately 30 minutes. Not for intravenous bolus administration or intramuscular administration.

2.2 Dosage for Perioperative Prophylaxis

Dosage for Perioperative Prophylaxis in Adults with Creatinine Clearance (CLcr) Equal to 55 mL/min or Greater
To prevent postoperative infection in contaminated or potentially contaminated surgery, recommended dosages are described in Table 1 below.

Table 1: Recommended Dosage for Perioperative Prophylaxis in Adults with CLcr Equal to 55 mL/min or Greater
Dose administered; ½ hour to 1 hour prior to the start; of surgery | Additional dose during lengthy operative procedures (e.g., 2 hours or more) | Dose for 24 hours postoperatively
1 gram (g) to 2 g | 500 mg to 1 g | 500 mg to 1 g every 6 hours to 8 hours

It is important that (i) the preoperative dose be given just prior (1/2 hour to 1 hour) to the start of surgery so that adequate antibacterial concentrations are present in the serum and tissues at the time of initial surgical incision and (ii) cefazolin be administered, if necessary, at appropriate intervals during surgery to provide sufficient concentrations of the antibacterial drug at the anticipated moments of greatest exposure to infective organisms.

The perioperative prophylactic administration of cefazolin should usually be discontinued within a 24-hour period after the surgical procedure. In surgery where the occurrence of infection may be particularly devastating (e.g., open-heart surgery and prosthetic arthroplasty), the prophylactic administration of cefazolin may be continued for 3 to 5 days following the completion of surgery.

Pediatric use information is approved for B. Braun Medical’s Cefazolin for Injection and Dextrose for Injection. However, due to B. Braun Medical’s marketing exclusivity rights, this drug product is not labeled with that pediatric information.

2.3 Preparation of Cefazolin for Injection

Parenteral drug products should be inspected visually for particulate matter and discoloration prior to administration, whenever solution and container permit. If particulate matter is evident in reconstituted fluids, the drug solutions should be discarded. Reconstituted solutions may range in color from pale yellow to yellow.

Reconstitution and Dilution

For intravenous infusion, reconstitute Cefazolin for Injection single-dose vials with Sterile Water for Injection according to Table 3 below and shake well. After reconstitution further dilute according to Table 3 using the following diluents:

For intermittent or continuous infusion: Dilute reconstituted Cefazolin for Injection in one of the following solutions:

- 0.9% Sodium Chloride Injection, USP
- 5% Dextrose Injection, USP

Discard unused portion.

Table 3: Volumes for Reconstitution and Dilution and Final Concentrations
Cefazolin for Injection Vial Contents | Amount of Sterile Water for Injection for Reconstitution | Approximate Reconstituted Concentrations | Recommended Diluent Volume | Approximate Final Concentrations
2 grams | 5 mL | 317 mg/mL | 50 mL | 40 mg/mL
2 grams | 5 mL | 317 mg/mL | 100 mL | 20 mg/mL
3 grams | 7.5 mL | 319 mg/mL | 100 mL | 30 mg/mL

Storage of Reconstituted and Diluted Solutions

When reconstituted or diluted according to the instructions above, Cefazolin for Injection is stable for 4 hours at room temperature or for 3 days if stored under refrigeration at 2°C to 8°C (36°F to 46°F).

3 DOSAGE FORMS AND STRENGTHS

Cefazolin for Injection: Supplied as 2 grams or 3 grams of cefazolin as a white to cream powder in a single-dose vial for reconstitution.

4 CONTRAINDICATIONS

4.1 Hypersensitivity to Cefazolin or the Cephalosporin Class of Antibacterial Drugs, Penicillins, or Other Beta-lactams

Cefazolin for Injection is contraindicated in patients who have a history of immediate hypersensitivity reactions (e.g., anaphylaxis, serious skin reactions) to cefazolin or the cephalosporin class of antibacterial drugs, penicillins, or other beta-lactams [see Warnings and Precautions (5.1)].

5 WARNINGS AND PRECAUTIONS

5.1 Hypersensitivity Reactions to Cefazolin, Cephalosporins, Penicillins, or Other Beta-lactams

Serious and occasionally fatal hypersensitivity (anaphylactic) reactions have been reported in patients receiving beta-lactam antibacterial drugs. Before therapy with Cefazolin for Injection is instituted, careful inquiry should be made to determine whether the patient has had previous immediate hypersensitivity reactions to cefazolin, cephalosporins, penicillins, or carbapenems. Exercise caution if this product is to be given to penicillin-sensitive patients because cross-hypersensitivity among beta-lactam antibacterial drugs has been clearly documented and may occur in up to 10% of patients with a history of penicillin allergy. If an allergic reaction to Cefazolin for Injection occurs, discontinue the drug.

5.2 Seizures in Patients with Renal Impairment

Seizures may occur with the administration of Cefazolin for Injection, particularly in patients with renal impairment when the dosage is not reduced appropriately. Discontinue Cefazolin for Injection if seizures occur or make appropriate dosage adjustments in patients with renal impairment [see Dosage and Administration (2.3)]. Anticonvulsant therapy should be continued in patients with known seizure disorders.

5.3 Clostridioides difficile-associated Diarrhea

Clostridioides difficile-associated diarrhea (CDAD) has been reported with use of nearly all antibacterial agents, including cefazolin for injection, and may range in severity from mild diarrhea to fatal colitis. Treatment with antibacterial agents alters the normal flora of the colon leading to overgrowth of C. difficile.

C. difficile produces toxins A and B, which contribute to the development of CDAD. Hypertoxin-producing isolates of C. difficile cause increased morbidity and mortality, as these infections can be refractory to antimicrobial therapy and may require colectomy. CDAD must be considered in all patients who present with diarrhea following antibacterial drug use. Careful medical history is necessary since CDAD has been reported to occur over two months after the administration of antibacterial agents.

If CDAD is suspected or confirmed, ongoing antibacterial drug use not directed against C. difficile may need to be discontinued. Appropriate fluid and electrolyte management, protein supplementation, antibacterial drug treatment of C. difficile, and surgical evaluation should be instituted as clinically indicated.

5.4 Risk of Development of Drug-resistant Bacteria

Prescribing Cefazolin for Injection in the absence of proven or strongly suspected bacterial infection or a prophylactic indication is unlikely to provide benefit to the patient and increases the risk of the development of drug-resistant bacteria.

As with other antimicrobials, prolonged use of Cefazolin for Injection may result in overgrowth of nonsusceptible microorganisms. Repeated evaluation of the patient's condition is essential. Should superinfection occur during therapy, appropriate measures should be taken.

5.5 Prothrombin Activity

Cefazolin for Injection may be associated with a fall in prothrombin activity. Those at risk include patients with renal or hepatic impairment or poor nutritional state, as well as patients receiving a protracted course of antimicrobial therapy, and patients previously stabilized on anticoagulant therapy. Prothrombin time should be monitored in patients at risk and exogenous vitamin K administered as indicated.

5.6 Drug/Laboratory Test Interactions

Urinary Glucose

The administration of cefazolin may result in a false-positive reaction with glucose in the urine when using glucose tests based on Benedict’s copper reduction reaction that determine the amount of reducing substances like glucose in the urine. It is recommended that glucose tests based on enzymatic glucose oxidase reactions be used.

Coombs’ Test

Positive direct Coombs' tests have been reported during treatment with cefazolin. In hematologic studies or in transfusion cross-matching procedures when antiglobulin tests are performed on the minor side or in Coombs' testing of newborns whose mothers have received cephalosporin antibacterial drugs before parturition, it should be recognized that a positive Coombs' test may be due to the drug.

6 ADVERSE REACTIONS

The following serious adverse reactions to cefazolin for injection are described below and elsewhere in the labeling:

• Hypersensitivity Reactions to Cefazolin, Cephalosporins, Penicillins, or Other Beta-lactams [see Warnings and Precautions (5.1)]

• Seizures in Patients with Renal Impairment [see Warnings and Precautions (5.2)]

• Clostridioides difficile-associated Diarrhea [see Warnings and Precautions (5.3)]

6.1 Clinical Trials Experience

Because clinical trials are conducted under widely varying conditions, adverse reaction rates observed in the clinical trials of a drug cannot be directly compared to rates in the clinical trials of another drug and may not reflect the rates observed in practice.

The following adverse reactions were reported from clinical trials:

Gastrointestinal: Diarrhea, oral candidiasis (oral thrush), mouth ulcers, vomiting, nausea, stomach cramps, epigastric pain, heartburn, flatus, anorexia and pseudomembranous colitis. Onset of pseudomembranous colitis symptoms may occur during or after antibacterial treatment [see Warnings and Precautions (5.3)].

Allergic: Anaphylaxis, eosinophilia, urticaria, itching, drug fever, skin rash, Stevens-Johnson syndrome.

Hematologic: Neutropenia, leukopenia, thrombocytopenia, thrombocythemia.

Hepatic: Transient rise in SGOT, SGPT, and alkaline phosphatase levels has been observed. Reports of hepatitis have been received.

Renal: Reports of increased BUN and creatinine levels, as well as renal failure, have been received.

Local Reactions: Instances of phlebitis have been reported at site of injection. Some induration has occurred.

Other Reactions: Pruritus (including genital, vulvar and anal pruritus, genital moniliasis, and vaginitis). Dizziness, fainting, lightheadedness, confusion, weakness, tiredness, hypotension, somnolence and headache.

Pediatric use information is approved for B. Braun Medical’s Cefazolin for Injection and Dextrose for Injection. However, due to B. Braun Medical’s marketing exclusivity rights, this drug product is not labeled with that pediatric information.

6.2 Postmarketing Experience

The following adverse reactions have been identified during post approval use of cefazolin. Because these reactions are reported voluntarily from a population of uncertain size, it is not always possible to reliably estimate their frequency or establish a causal relationship to drug exposure.

Immune system disorders: Serum sickness-like reaction

Renal and urinary disorders: Acute tubulointerstitial nephritis (ATIN)

Skin and subcutaneous tissue disorders: Acute generalized exanthematous pustulosis (AGEP)

6.3 Cephalosporin-class Adverse Reactions

In addition to the adverse reactions listed above that have been observed in patients treated with cefazolin, the following adverse reactions and altered laboratory tests have been reported for cephalosporin-class antibacterials: Stevens-Johnson syndrome, erythema multiforme, toxic epidermal necrolysis, renal impairment, toxic nephropathy, aplastic anemia, hemolytic anemia, hemorrhage, a fall in prothrombin activity, hepatic impairment including cholestasis, and pancytopenia.

7 DRUG INTERACTIONS

The renal excretion of cefazolin is inhibited by probenecid. Co-administration of probenecid with Cefazolin for Injection is not recommended.

8 USE IN SPECIFIC POPULATIONS

8.1 Pregnancy

Risk Summary

Available data from published prospective cohort studies, case series and case reports over several decades with cephalosporin use, including cefazolin, in pregnant women have not established a drug-associated risk of major birth defects, miscarriage, or adverse maternal or fetal outcomes. Cefazolin crosses the placenta.

Animal reproduction studies with rats, mice and rabbits administered cefazolin during organogenesis at doses 1 to 3 times the maximum recommended human dose (MRHD) did not demonstrate adverse developmental outcomes. In rats subcutaneously administered cefazolin prior to delivery and throughout lactation, there were no adverse effects on offspring at a dose approximately 2 times the MRHD (see Data).

The estimated background risk of major birth defects and miscarriage for the indicated population is unknown. All pregnancies have a background risk of birth defect, loss, or other adverse outcomes. In the U.S. general population, the estimated background risk of major birth defects and miscarriage in clinically recognized pregnancies is 2% to 4% and 15% to 20%, respectively.

Data

Human Data

While available studies cannot definitively establish the absence of risk, published data from case-control studies and case reports over several decades have not identified an association with cephalosporin use during pregnancy and major birth defects, miscarriage, or other adverse maternal or fetal outcomes. Available studies have methodologic limitations, including small sample size, retrospective data collection, and inconsistent comparator groups.

Animal Data

Reproduction studies have been performed in rats, mice and rabbits administered cefazolin during organogenesis at doses of 2000, 4000 and 240 mg/kg/day (approximately 1 to 3 times the maximum recommended human dose on a body surface area comparison). There was no evidence of any adverse effects on embryofetal development due to cefazolin. In a peripostnatal study in rats, cefazolin administered subcutaneously up to 1200 mg/kg/day (approximately 2 times the MRHD based on body surface area comparison) to pregnant dams prior to delivery and through lactation caused no adverse effects on offspring.

8.2 Lactation

Data from published literature report that cefazolin is present in human milk but is not expected to accumulate in a breastfed infant. There are no data on the effects of cefazolin on the breastfed child or on milk production.

The developmental and health benefits of breastfeeding should be considered along with the mother’s clinical need for Cefazolin for Injection and any potential adverse effects on the breastfed child from Cefazolin for Injection or from the mother’s underlying condition.

8.4 Pediatric Use

Safety and effectiveness of Cefazolin for Injection for perioperative prophylaxis have not been established for pediatric patients less than 10 years or weighing less than 50 kg.

The safety and effectiveness of Cefazolin for Injection in premature infants and neonates have not been established and is not recommended for use in this age group of pediatric patients.

Pediatric use information is approved for B. Braun Medical’s Cefazolin for Injection and Dextrose for Injection. However, due to B. Braun Medical’s marketing exclusivity rights, this drug product is not labeled with that pediatric information.

8.5 Geriatric Use

Of the 920 subjects who received cefazolin in clinical studies, 313 (34%) were 65 years and over, while 138 (15%) were 75 years and over. No overall differences in safety or effectiveness were observed between these subjects and younger subjects. Other reported clinical experience has not identified differences in responses between the elderly and younger patients, but greater sensitivity of some older individuals cannot be ruled out.

This drug is known to be substantially excreted by the kidney, and the risk of toxic reactions to this drug may be greater in patients with impaired renal function. Because elderly patients are more likely to have decreased renal function, care should be taken in dose selection, and it may be useful to monitor renal function [see Dosage and Administration (2.3) and Warnings and Precautions (5.2)].

8.6 Renal Impairment

When Cefazolin for Injection is administered to adult patients with low urinary output because of impaired renal function (creatinine clearance less than 55 mL/min. for adult patients), lower daily dosage is required [see Dosage and Administration (2.3) and Warnings and Precautions (5.2)].

10 OVERDOSAGE

Accidental overdosage resulting in seizures may occur in patients with renal impairment who receive doses greater than the recommended dosage of Cefazolin for Injection [see Warnings and Precautions (5.2)]. If seizures associated with accidental overdosage occur, discontinue Cefazolin for Injection and give supportive treatment.

11 DESCRIPTION

Cefazolin for Injection USP is a semi-synthetic cephalosporin for parenteral administration. It is the sodium salt of 3-{[(5-methyl-1,3,4-thiadiazol-2-yl)thio]-methyl}-8-oxo-7-[2-(1H-tetrazol-1-yl)acetamido]-5-thia-1-azabicyclo [4.2.0]oct‑2-ene-2-carboxylic acid.

Structural Formula:

C14H13N8NaO4S3 M.W. 476.5

Cefazolin for Injection is supplied as a sterile powder in single-dose vials.

The 2 g/vial Cefazolin for Injection contains 2 grams of cefazolin (equivalent to 2.097 g of cefazolin sodium). The 3 g/vial Cefazolin for Injection contains 3 grams of cefazolin (equivalent to 3.144 grams of cefazolin sodium).

Each vial contains 48 mg of sodium per gram of cefazolin sodium.

After reconstitution with sterile water for injection, the drug product solution has a pH of 4.0 to 6.0.

Cefazolin for Injection is intended for intravenous infusion.

12 CLINICAL PHARMACOLOGY

12.1 Mechanism of Action

Cefazolin is an antibacterial drug [see Microbiology (12.4)].

12.2 Pharmacodynamics

The pharmacokinetic/pharmacodynamic relationship for cefazolin has not been evaluated in patients.

12.3 Pharmacokinetics

Studies have shown that following intravenous administration of cefazolin to normal volunteers, mean serum concentrations peaked at approximately 185 mcg/mL and were approximately 4 mcg/mL at 8 hours for a 1 gram dose.

In a study of constant intravenous infusion with dosages of 3.5 mg/kg for 1 hour (approximately 250 mg) and 1.5 mg/kg the next 2 hours (approximately 100 mg) in healthy volunteers, cefazolin serum concentrations at the third hour were approximately 28 mcg/mL.

Plasma pharmacokinetic parameters of cefazolin in healthy volunteers (N=12) following a single 15-minute IV infusion of 2 grams of Cefazolin for Injection are summarized in Table 4.

Table 4: Mean (Standard Deviation) Plasma Pharmacokinetic Parameters of Cefazolin in Healthy Volunteers
 | N | Cmax (mcg/mL) | Tmax*; (h) | AUC0-inf (mcg*h/mL) | t1/2; (h) | CL (L/h) | Vz (L)
Single 2 grams Dose as a 15-Minute IV Infusion | 12 | 280.9 (45.9) | 0.25; (0.25-0.33) | 509.9 (89.3) | 2.01 (0.28) | 4.03 (0.68) | 11.50 (1.53)

*Tmax reported as median (range)

N= number of subjects observed; Cmax = maximum plasma concentration; Tmax = time to maximum plasma concentration; AUC0-inf = area under the plasma concentration-time curve extrapolated to infinity; t1/2 = apparent plasma terminal elimination half-life; CL = total clearance; Vz = volume of distribution

Studies in patients hospitalized with infections indicate that cefazolin produces mean peak serum concentrations approximately equivalent to those seen in normal volunteers.

Distribution

Bile concentrations in patients without obstructive biliary disease can reach or exceed serum concentrations by up to five times; however, in patients with obstructive biliary disease, bile concentrations of cefazolin are considerably lower than serum concentrations (less than 1 mcg/mL).

In synovial fluid, the cefazolin concentration becomes comparable to that reached in serum at about 4 hours after drug administration.

Studies of cord blood show prompt transfer of cefazolin across the placenta. Cefazolin is present in very low concentrations in the milk of nursing mothers.

Elimination

The serum half-life for cefazolin is approximately 1.8 hours following IV administration.

Excretion

Cefazolin is excreted unchanged in the urine. In the first 6 hours approximately 60% of the drug is excreted in the urine and this increases to 70% to 80% within 24 hours.

Pediatric use information is approved for B. Braun Medical’s Cefazolin for Injection and Dextrose for Injection. However, due to B. Braun Medical’s marketing exclusivity rights, this drug product is not labeled with that pediatric information.

12.4 Microbiology

Mechanism of Action

Cefazolin is a bactericidal agent that acts by inhibition of bacterial cell wall synthesis.

Resistance

Predominant mechanisms of bacterial resistance to cephalosporins include the presence of extended-spectrum beta-lactamases and enzymatic hydrolysis.

Antimicrobial Activity

Cefazolin has been shown to be active against most isolates of the following microorganisms, both in vitro and in clinical infections [see Indications and Usage (1)]:

Aerobic bacteria

Gram-Positive Bacteria

Staphylococcus aureus
Staphylococcus epidermidis
Streptococcus agalactiae
Streptococcus pneumoniae
Streptococcus pyogenes

Methicillin-resistant staphylococci are uniformly resistant to cefazolin.

Gram-Negative Bacteria

Escherichia coli
Proteus mirabilis

Most isolates of indole positive Proteus (Proteus vulgaris), Enterobacter spp., Morganella morganii, Providencia rettgeri, Serratia spp., and Pseudomonas spp. are resistant to cefazolin.

Susceptibility Testing

For specific information regarding susceptibility test interpretive criteria and associated test methods and quality control standards recognized by FDA for this drug, please see: https://www.fda.gov/STIC.

13 NONCLINICAL TOXICOLOGY

13.1 Carcinogenesis, Mutagenesis, Impairment of Fertility

Carcinogenesis and Mutagenesis

Mutagenicity studies and long-term studies in animals to determine the carcinogenic potential of Cefazolin for Injection have not been performed.

Impairment of Fertility

Fertility studies conducted in rats subcutaneously administered cefazolin at doses of 2000 mg/kg/day (approximately 3 times the maximum recommended human dose based on body surface area comparison) showed no impairment of mating and fertility.

16 HOW SUPPLIED/STORAGE AND HANDLING

Cefazolin for Injection is available in a single-dose vial containing 2 grams or 3 grams of cefazolin as a white to cream powder for reconstitution. Each vial contains cefazolin sodium equivalent to 2 grams or 3 grams of cefazolin, and is supplied as follows:

2 grams per Single-Dose Vial: NDC 44567-840-01

Carton of 25: NDC 44567-840-25

3 grams per Single-Dose Vial: NDC 44567-845-01

Carton of 25: NDC 44567-845-25

Store Cefazolin for Injection vials at 20°C to 25°C (68°F to 77°F) [see USP Controlled Room Temperature]. Protect from Light.

Storage conditions for the reconstituted and diluted solutions are described elsewhere in labeling [see Dosage and Administration (2.4)].

17 PATIENT COUNSELING INFORMATION

Serious Allergic Reactions

Advise patients that allergic reactions, including serious allergic reactions could occur and that serious reactions require immediate treatment and discontinuation of Cefazolin for Injection. Patients should report to their health care provider any previous allergic reactions to cefazolin, cephalosporins, penicillins, or other similar antibacterials [see Warnings and Precautions (5.1)].

Seizures

Advise patients that seizures could occur with Cefazolin for Injection. Instruct patients to inform a healthcare provider at once of any signs and symptoms of seizures, for immediate treatment, dosage adjustment, or discontinuation of Cefazolin for Injection [see Warnings and Precautions (5.2)].

Diarrhea

Advise patients that diarrhea is a common problem caused by antibacterials including cefazolin for injection, which usually ends when the antibacterial is discontinued. Sometimes after starting treatment with antibacterials, including Cefazolin for Injection, patients can develop watery and bloody stools (with or without stomach cramps and fever) even as late as two or more months after having taken the last dose of the antibacterials. If this occurs, patients should contact a physician as soon as possible [see Warnings and Precautions (5.3)].

Antibacterial Resistance

Patients should be counseled that antibacterial drugs, including Cefazolin for Injection should only be used to treat bacterial infections. They do not treat viral infections (e.g., the common cold). When Cefazolin for Injection is prescribed to treat a bacterial infection, patients should be told that although it is common to feel better early in the course of therapy, the medication should be taken exactly as directed. Skipping doses or not completing the full course of therapy may (1) decrease the effectiveness of the immediate treatment and (2) increase the likelihood that bacteria will develop resistance and will not be treatable by Cefazolin for Injection or other antibacterial drugs in the future [see Warnings and Precautions (5.4)].

Manufactured for:

WG Critical Care, LLC

Paramus, NJ 07652

Made in Italy

PACKAGE/LABEL PRINCIPAL DISPLAY PANEL

NDC 44567-840-01

Cefazolin for Injection, USP 2 grams per vial

For Intravenous Infusion Only.

PACKAGE/LABEL PRINCIPAL DISPLAY PANEL

NDC 44567-845-01

Cefazolin for Injection, USP 3 grams per vial

For Intravenous Infusion Only.